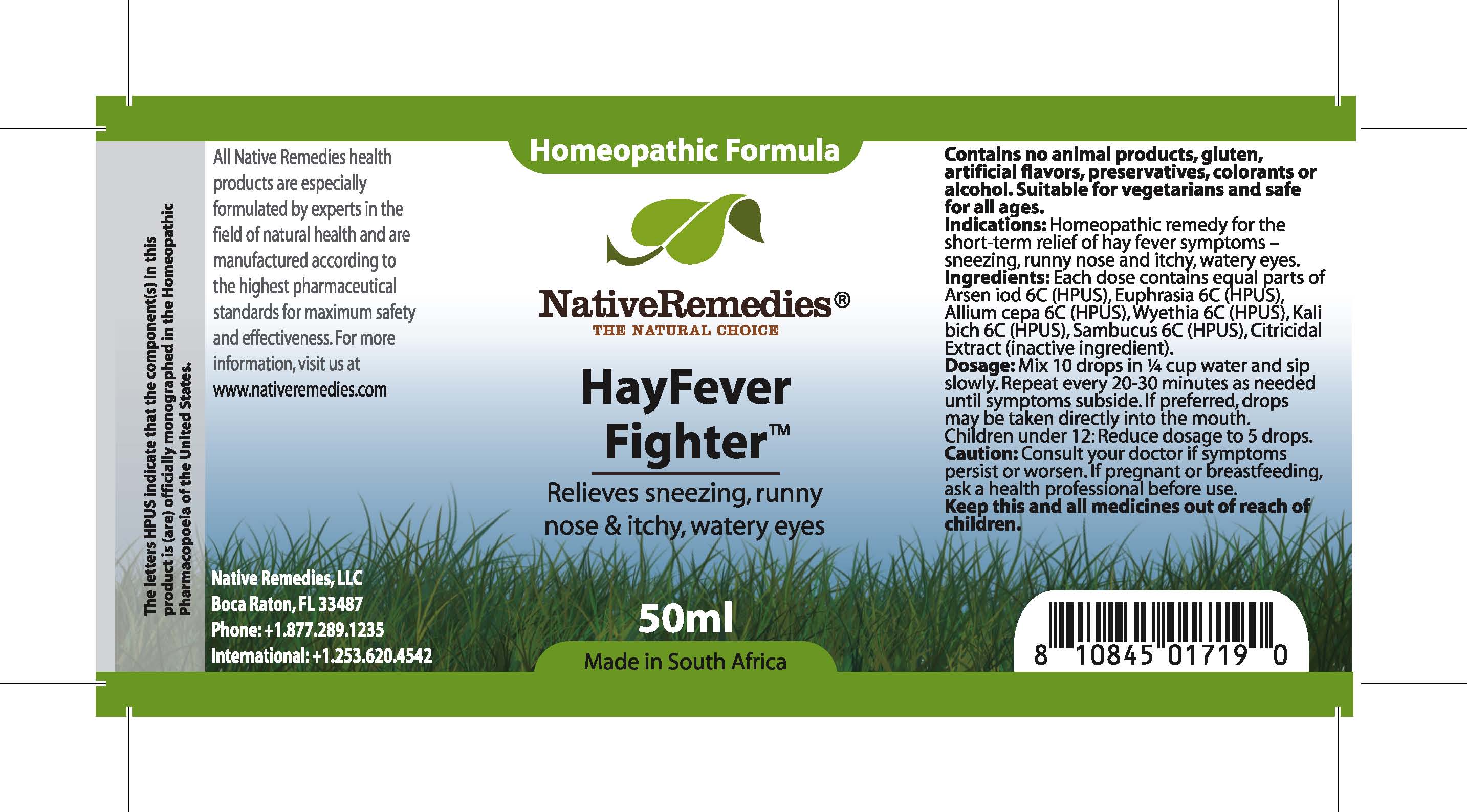 DRUG LABEL: HayFever Fighter
NDC: 68647-167 | Form: TINCTURE
Manufacturer: Feelgood Health
Category: homeopathic | Type: HUMAN OTC DRUG LABEL
Date: 20100728

ACTIVE INGREDIENTS: ARSENIC TRIIODIDE 6 [hp_C]/33.3 mL; EUPHRASIA STRICTA 6 [hp_C]/33.3 mL; ONION 6 [hp_C]/33.3 mL; WYETHIA HELENIOIDES ROOT 6 [hp_C]/33.3 mL; POTASSIUM DICHROMATE 6 [hp_C]/33.3 mL; AMERICAN ELDERBERRY 6 [hp_C]/33.3 mL
INACTIVE INGREDIENTS: CITRUS PARADISI SEED 0.125 mL/50 mL; WATER 49.486 mL/50 mL

HAYFEVER FIGHTER

PURPOSE

Relieves sneezing, runny nose and itchy, watery eyes

INDICATIONS AND USAGE

Indications: Homeopathic remedy for the relief of hay fever symptoms – sneezing, runny nose and itchy, watery eyes.

DOSAGE AND ADMINISTRATION

Dosage: Mix 10 drops in ¼ cup water and sip slowly. Repeat every 20-30 minutes as needed until symptoms subside. If preferred, drops may be taken directly into the mouth. Children under 12: Reduce dosage to 5 drops.

GENERAL PRECAUTIONS

Caution: Consult your doctor if symptoms persist or worsen. Keep this and all medicines out of reach of children.

ACTIVE INGREDIENT

Ingredients: Each dose contains equal parts of Arsen iod (6C) (HPUS), Euphrasia (6C) (HPUS), Allium cepa (6C) (HPUS), Wyethia (6C) (HPUS), Kali bich (6C) (HPUS), Sambucus (6C) (HPUS)

Citricidal Extract (inactive ingredient).

PREGNANCY

If pregnant or breastfeeding, ask a health professional before use.

WARNINGS

Contains no animal products, gluten, artificial flavors, preservatives, colorants or alcohol. Suitable for vegetarians and safe for all ages.

PATIENT COUNSELING INFORMATION

All Native Remedies health products are especially formulated by experts in the field of natural health and are manufactured according to the highest pharmaceutical standards for maximum safety and effectiveness. For more information, visit us at www.nativeremedies.com

Distributed by

Native Remedies, LLC

6531 Park of Commerce Blvd.

Suite 160

Boca Raton, FL 33487

Phone: 1.877.289.1235

The letters HPUS indicate that the component(s) in this product is (are) officially monographed in the Homeopathic Pharmacopoeia of the United States.

KEEP OUT OF REACH OF CHILDREN

Keep this and all medicines out of reach of children.